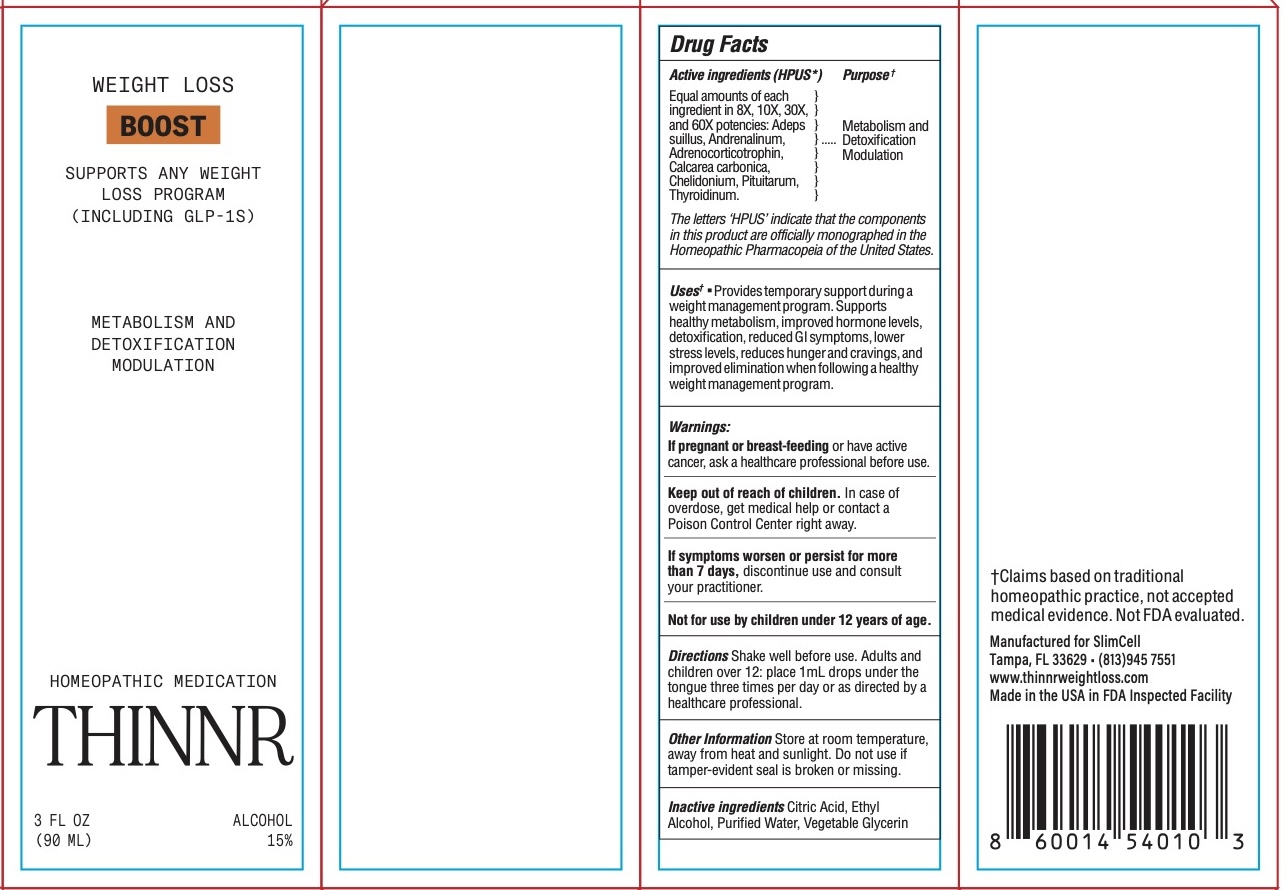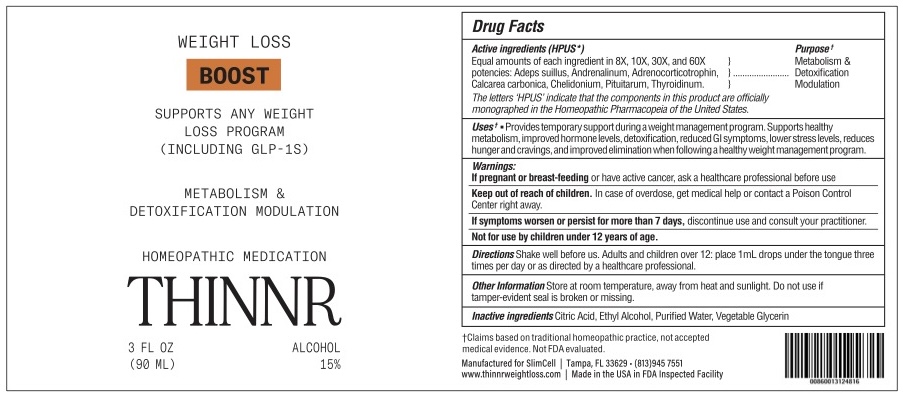 DRUG LABEL: Thinnr BOOST
NDC: 85095-200 | Form: LIQUID
Manufacturer: SLIMCELL, LLC
Category: homeopathic | Type: HUMAN OTC DRUG LABEL
Date: 20250820

ACTIVE INGREDIENTS: ADEPS SUILLUS 8 [hp_X]/1 mL; THYROID 8 [hp_X]/1 mL; SUS SCROFA PITUITARY GLAND, POSTERIOR 8 [hp_X]/1 mL; CHELIDONIUM MAJUS 8 [hp_X]/1 mL; OYSTER SHELL CALCIUM CARBONATE, CRUDE 8 [hp_X]/1 mL; CORTICOTROPIN 8 [hp_X]/1 mL; EPINEPHRINE 8 [hp_X]/1 mL
INACTIVE INGREDIENTS: CITRIC ACID; ALCOHOL; WATER; GLYCERIN

Thinnr BOOST

HPUS Active Ingredients: Equal amounts of each ingredient in 8X, 10X, 30X, and 60X potencies: Adeps suillus, Andrenalinum, Adrenocorticotrophin, Calcarea carbonica, Chelidonium, Pituitarum, and Thyroidinum.

Uses*:

Uses*: Provides temporary support during a weight management program. Supports healthy metabolism, improved hormone levels, detoxification, lower stress levels, reduces hunger and cravings, and improved elimination when following a healthy weight management program.

Warnings

Warnings: If symptoms worsen or persist for more than 7 days, discontinue use and consult your practitioner.

Directions

Shake well before us. Adults and children over 12: place 1mL drops under the tongue three times per day or as directed by a healthcare professional.

Other Information

Store at room temperature, away from heat and sunlight.
Do not use if tamper-evident seal is broken or missing.

Inactive Ingredients

Inactive Ingredients: Ethyl Alcohol, Glycerin, Purified Water.

Keep out of reach of children. In case of overdose, get medical help or contact a Poison Control Center right away.

If pregnant or breast-feeding or have active cancer, ask a healthcare professional before use

PURPOSE

Metabolism and detoxification modulation